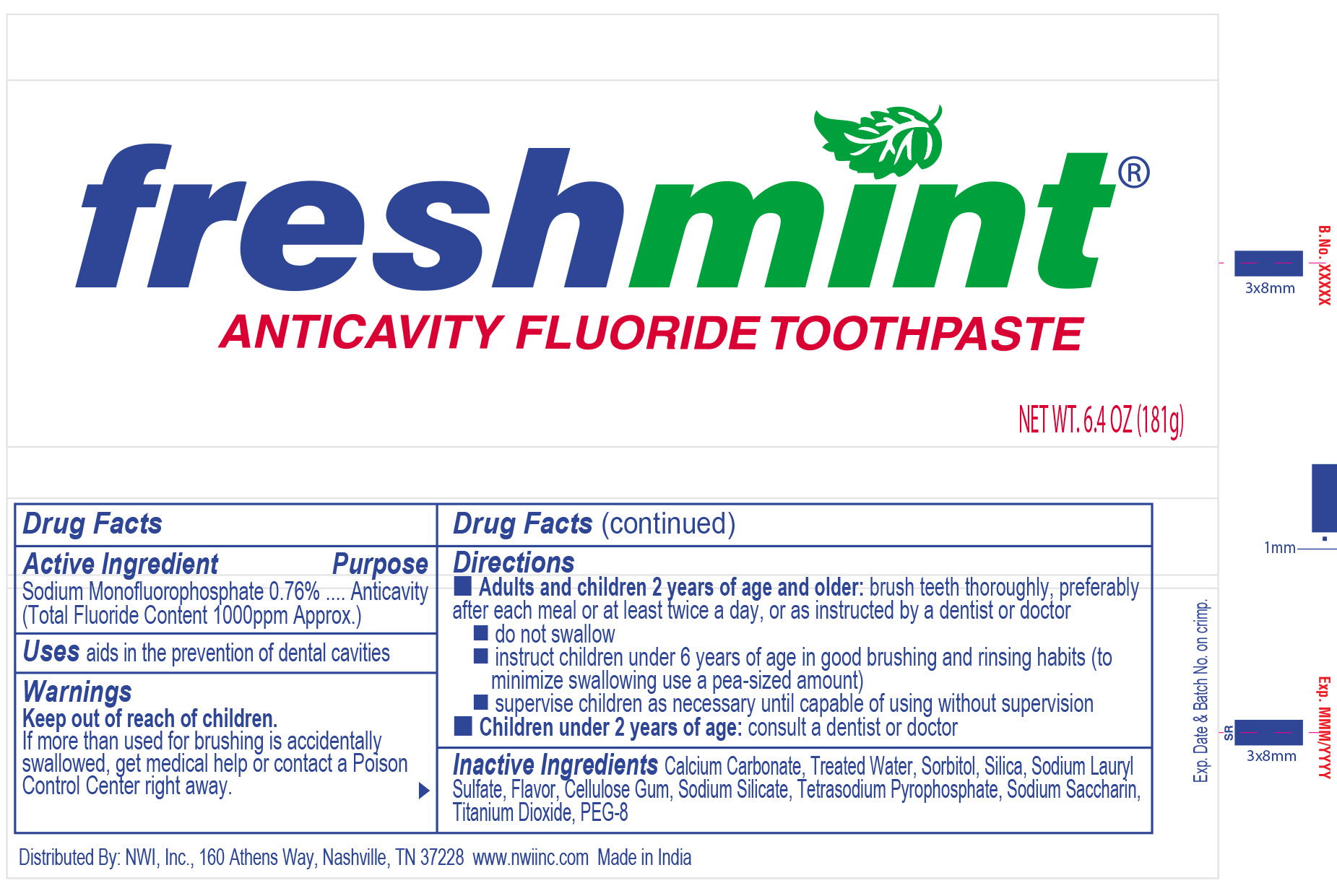 DRUG LABEL: Freshmint Anticavity Fluoride
NDC: 51824-067 | Form: PASTE, DENTIFRICE
Manufacturer: New World Imports, Inc
Category: otc | Type: HUMAN OTC DRUG LABEL
Date: 20251201

ACTIVE INGREDIENTS: SODIUM MONOFLUOROPHOSPHATE 7.6 mg/1 g
INACTIVE INGREDIENTS: CALCIUM CARBONATE; WATER; SORBITOL; SILICON DIOXIDE; SODIUM LAURYL SULFATE; CARBOXYMETHYLCELLULOSE SODIUM; SODIUM SILICATE; SODIUM PYROPHOSPHATE; SACCHARIN SODIUM; TITANIUM DIOXIDE; POLYETHYLENE GLYCOL 400

Drug Facts

ACTIVE INGREDIENT

Sodium Monofluorophosphate - .76%

(Total Fluoride Content - 1000 ppm Approx.)

PURPOSE

Anticavity

Keep out of Reach of Children.

If more than used for brushing is accidentally swallowed, get medical help or contact a Poison Control Center right away.

INDICATIONS AND USAGE

Aids in the prevention of dental cavities

Keep out of Reach of Children.

If more than used for brushing is accidentally swallowed, get medical help or contact a Poison Control Center right away.

DOSAGE AND ADMINISTRATION

Adults and Children 2 years of age and older: Brush teeth thoroughly, preferably after each meal or at least twice a day, or as instructed by a dentist or doctor.

- do not swallow
- instruct children under 6 years of age in good brushing and rinsing habits (to minimize swallowing use a pea-sized amount)
- supervise children as necessary until capable of using without supervision

Children under 2 years of age:consult a dentist or doctor

INACTIVE INGREDIENT

Calcium Carbonate, Treated Water, Sorbitol, Silica, Sodium Lauryl Sulfate, Flavor, Cellulose Gum, Sodium Silicate, Tetrasodium Pyrophosphate, Sodium Saccharin, Titanium Dioxide, PEG-8